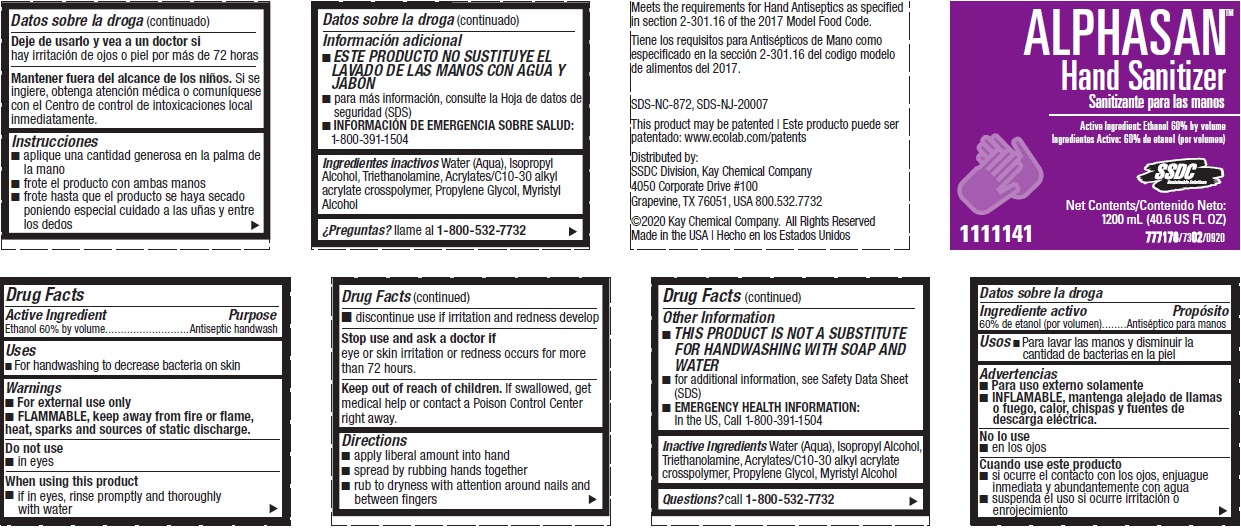 DRUG LABEL: SSDC Alphasan Hand Sanitizer
NDC: 47593-680 | Form: SOLUTION
Manufacturer: Ecolab Inc.
Category: otc | Type: HUMAN OTC DRUG LABEL
Date: 20251231

ACTIVE INGREDIENTS: ALCOHOL 60 mL/100 mL
INACTIVE INGREDIENTS: WATER; ISOPROPYL ALCOHOL; TROLAMINE; CARBOMER COPOLYMER TYPE B (ALLYL PENTAERYTHRITOL CROSSLINKED); PROPYLENE GLYCOL; MYRISTYL ALCOHOL

Drug Facts

Active ingredient

Ethanol 60% by volume

Purpose

Antiseptic Handwash

Uses

- For handwashing to decrease bacteria on skin

Warnings

- For external use only
- Flammable, keep away from fire or flame, heat, sparks and sources of static discharge.

Do not use

- In eyes

When using this product

- If in eyes, rinse promptly and thoroughly with water
- Discontinue use if irritation and redness develop

Stop use and ask a doctor if

- Eye or skin irritation or redness occurs for more than 72 hours

Keep out of reach of children. If swallowed, get medical help or contact a Poison Control Center right away.

Directions

- Apply liberal amount into hand
- Spread by rubbing hands together
- Rub to dryness with attention to area around nails and between fingers

Other information

- THIS PRODUCT IS NOT A SUBSTITUTE FOR HANDWASHING WITH SOAP AND WATER
- for additional information, see Safety Data Sheet (SDS)
- for emergency medical information in USA, call 1-800-391-1504

Inactive Ingredients

water (aqua), isopropyl alcohol, triethanolamine, acrylates/C10-30 alkyl acrylate crosspolymer, propylene glycol, myristyl alcohol

Questions? call 1-800-532-7732

Principal display panel and representative label

SSDC ALPHASAN

Hand Sanitizer

Active Ingredient: Ethanol 60% by volume

1111141

Net Contents

1200 mL (40.6 US FL OZ)

SDS-NC-872, SDS-NJ-20007

Distributed by:

SSDC Division, Kay Chemical Company

4050 Corporate Drive #100

Grapevine, TX 76051, USA 800.532.7732

©2020 Kay Chemical Company. All Rights Reserved Made in United States | Hecho en Estados Unidos

777178/7302/0920